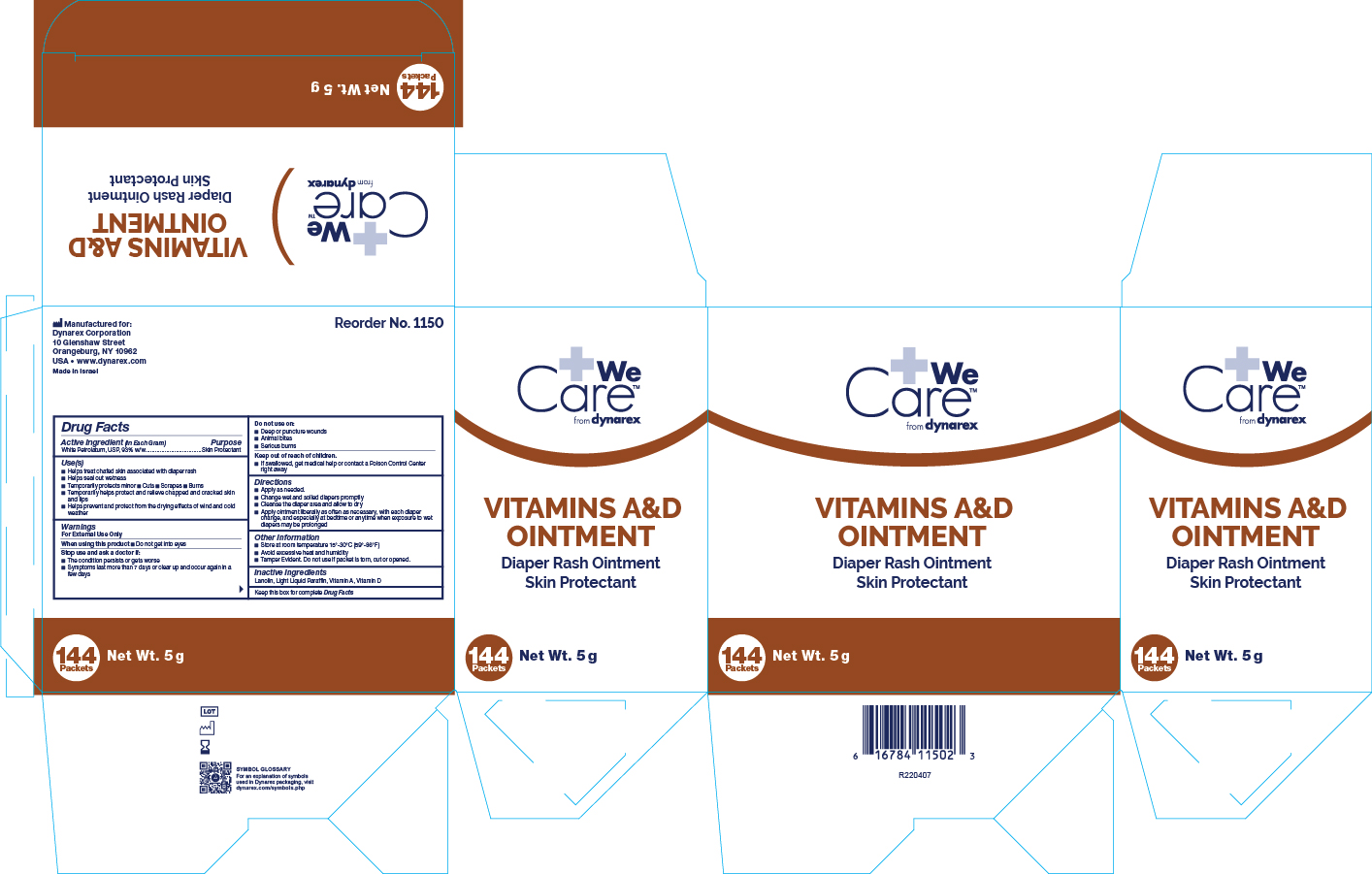 DRUG LABEL: Vitamin A D
NDC: 67777-215 | Form: OINTMENT
Manufacturer: Dynarex Corporation
Category: otc | Type: HUMAN OTC DRUG LABEL
Date: 20251218

ACTIVE INGREDIENTS: PETROLATUM 93 g/100 g
INACTIVE INGREDIENTS: LANOLIN; VITAMIN D; LIGHT MINERAL OIL; VITAMIN A PALMITATE

1150 Vitamins A&D Ointment

Active Ingredient

White Petrolatum, USP, 93% w/w

Purpose

Skin Protectant

Use(s)

• Helps treat chafed skin associated with diaper rash

• Helps seal out wetness

• Temporarily protects minor • Cuts • Scrapes • Burns

• Temporarily helps protext and relieve chapped and cracked skin and lips

• Helps prevent and protect from the drying effects of wind and cold weather

Warnings

For External Use Only

When using this product

• Do not get into eyes

Stop use and ask a doctor if

• The condition persists or gets worse

• Symptoms last more than 7 days or clear up and occur again in a few days

Do not use on

• Deep or puncture wounds

• Animal bites

• Serious burns

Keep out of reach of children

• If swallowed, get medical help or contact a Poison Control Center right away

Directions

• Apply as needed

• Change wet and soiled diapers promptly

• Cleanse the diaper area and allow to dry

• Apply ointment liberally as often as necessary, with each diaper change, and especially at bedtime or anytime when exposure to wet

diapers may be prolonged.

Other Information

• Store at room temperature 15º-30ºC (59°-86°F)

• Avoid excessive heat and humidity

• Tamper Evident. Do not use if packet is torn, cut or opened.

Inactive Ingredients

Lanolin, Light Liquid Paraffin, Vitamin A, Vitamin D

Label

1150 Vitamin A&D Ointment